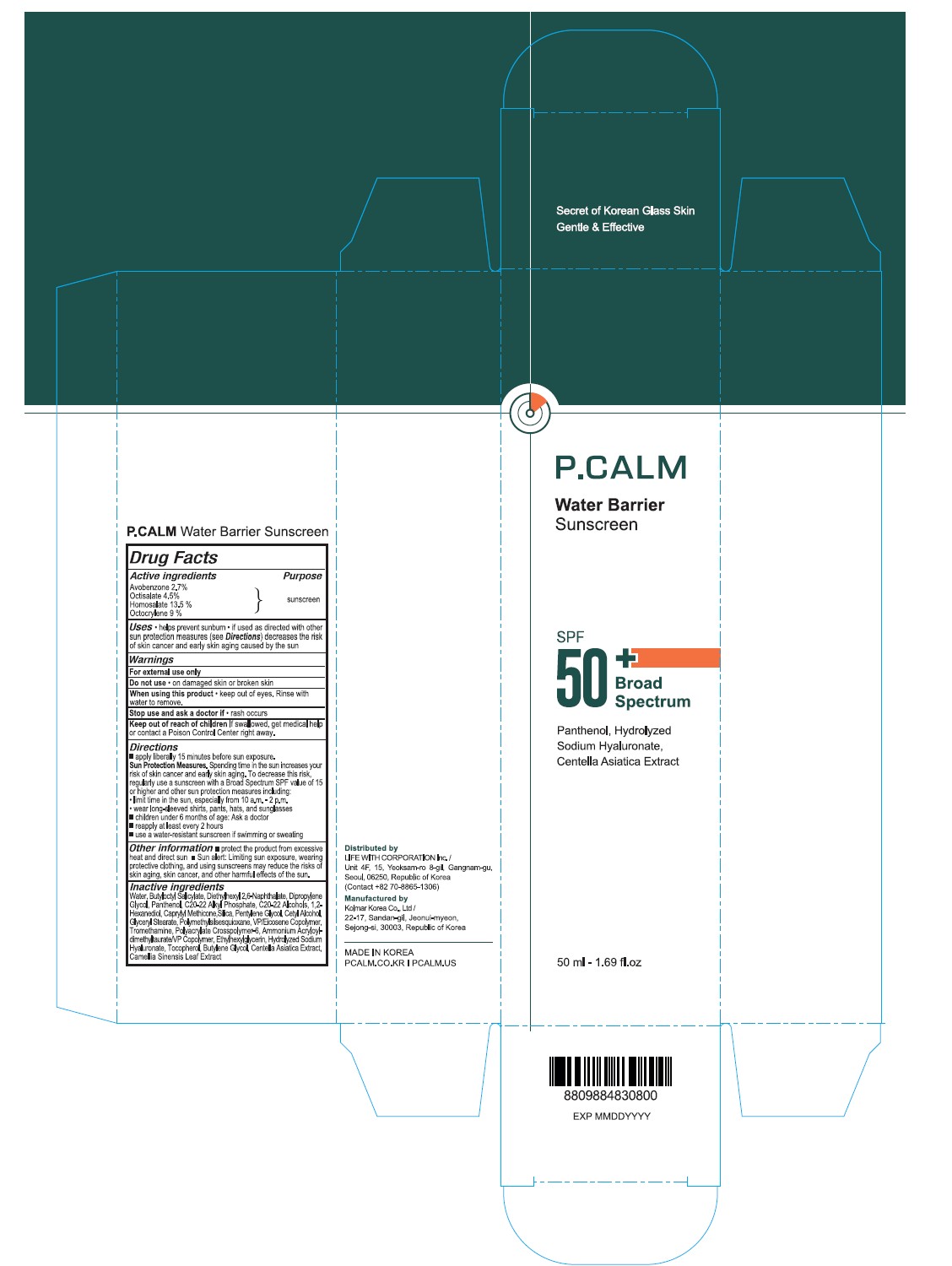 DRUG LABEL: P.CALM Water Barrier Sunscreen SPF 50 Broad Spectrum
NDC: 83735-002 | Form: LOTION
Manufacturer: LIFE WITHCORPORATION Inc.
Category: otc | Type: HUMAN OTC DRUG LABEL
Date: 20251201

ACTIVE INGREDIENTS: AVOBENZONE 2.7 g/100 mL; OCTISALATE 4.5 g/100 mL; OCTOCRYLENE 9 g/100 mL; HOMOSALATE 13.5 g/100 mL
INACTIVE INGREDIENTS: ETHYLHEXYLGLYCERIN; TOCOPHEROL; CENTELLA ASIATICA; PANTHENOL; 1,2-HEXANEDIOL; TROMETHAMINE; CETYL ALCOHOL; SODIUM HYALURONATE; C20-22 ALCOHOLS; POLYMETHYLSILSESQUIOXANE (4.5 MICRONS); PENTYLENE GLYCOL; CAPRYLYL METHICONE; CAMELLIA SINENSIS LEAF; C20-22 ALKYL PHOSPHATE; DIETHYLHEXYL 2,6-NAPHTHALATE; DIPROPYLENE GLYCOL; GLYCERYL STEARATE; POLYACRYLATE CROSSPOLYMER-6; AMMONIUM ACRYLOYLDIMETHYLTAURATE/VP COPOLYMER; BUTYLENE GLYCOL; BUTYLOCTYL SALICYLATE; SILICA; VINYLPYRROLIDONE/EICOSENE COPOLYMER

P.CALM Water Barrier Sunscreen SPF 50+ Broad Spectrum

ACTIVE INGREDIENT

Avobenzone 2.7%

Octisalate 4.5%

Homosalate13.5%

Octocrylene 9%

PURPOSE

sunscreen

INDICATIONS AND USAGE

- helps prevent sunburn
- if used as directed with other sun protection (see Directions) decreases the risk of skin cancer and early skin aging caused by the sun

WARNINGS

For external use only

Do not use

- on damaged skin or broken skin

When using this product

- keep out of eyes. Rinse with water to remove

Stop use and ask a doctor if rash occurs

- rash occurs

Keep out of reach of children

If swallowed, get medical help or contact a Poison Control Center right away

DOSAGE AND ADMINISTRATION

- apply liberally 15 minutes before sun exposure

Sun Protection Measures. Spending time in the sun increases your risk of skin cancer and early skin aging. To decrease this risk, regularly use a sunscreen with a Broad Spectrum SPF value of 15 or higher and other sun protection measures including: • limit time in the sun, especially from 10 a.m.-2 p.m. • wear long-sleeved shirts, pants, hats, and sunglasses

- children under 6 months of age: Ask a doctor
- reapply at least every 2 hours
- use a water resistant sunscreen if swimming or sweating

- protect the product from excessive heat and direct sun
- Sun alert: Limiting sun exposure, wearing protective clothing, and using sunscreens may reduce the risks of skin aging, skin cancer, and other harmful effects of the sun

INACTIVE INGREDIENT

Water, Butyloctyl Salicylate, Diethylhexyl 2,6-Naphthalate, Dipropylene Glycol, Panthenol, C20-22 Alkyl Phosphate, C20-22 Alcohols, 1,2-Hexanediol, Caprylyl Methicone, Silica, Pentylene Glycol, Cetyl Alcohol, Glyceryl Stearate, Polymethylsilsesquioxane, VP/Eicosene Copolymer,Tromethamine, Polyacrylate Crosspolymer-6, Ammonium Acryloyldimethyltaurate/VP Copolymer, Ethylhexylglycerin, Hydrolyzed Sodium Hyaluronate, Tocopherol, Butylene Glycol, Centella Asiatica Extract, Camellia Sinensis Leaf Extract

PACKAGE LABEL

P.CALM Water Barrier Sunscreen

SPF 50+ Broad Spectrum

Panthenol, Hydrolyzed Sodium Hyaluronate, Centella Asiatica Extract

50mL - 1.69 fl.ox

PACKAGE LABEL

P.CALM Water Barrier Sunscreen

SPF 50+ Broad Spectrum

Panthenol, Hydrolyzed Sodium Hyaluronate, Centella Asiatica Extract

50 ml - 1.69 fl.oz